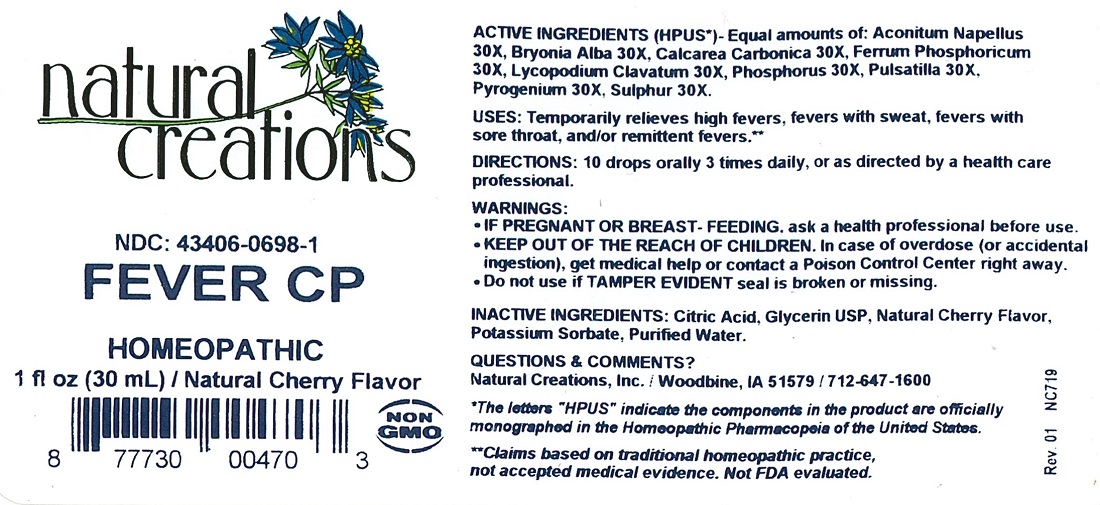 DRUG LABEL: Fever CP
NDC: 43406-0698 | Form: LIQUID
Manufacturer: Natural Creations, Inc
Category: homeopathic | Type: HUMAN OTC DRUG LABEL
Date: 20181221

ACTIVE INGREDIENTS: ACONITUM NAPELLUS WHOLE 30 [hp_X]/1 mL; BRYONIA ALBA ROOT 30 [hp_X]/1 mL; OYSTER SHELL CALCIUM CARBONATE, CRUDE 30 [hp_X]/1 mL; FERROSOFERRIC PHOSPHATE 30 [hp_X]/1 mL; LYCOPODIUM CLAVATUM SPORE 30 [hp_X]/1 mL; PHOSPHORUS 30 [hp_X]/1 mL; PULSATILLA VULGARIS WHOLE 30 [hp_X]/1 mL; RANCID BEEF 30 [hp_X]/1 mL; SULFUR 30 [hp_X]/1 mL
INACTIVE INGREDIENTS: CITRIC ACID MONOHYDRATE; GLYCERIN; POTASSIUM SORBATE; WATER

Fever CP

ACTIVE INGREDIENT

ACTIVE INGREDIENTS (*HPUS) - Equal amounts of: Aconitum Napellus 30X, Bryonia Alba 30X, Calcarea Carbonica 30X, Ferrum Phosphoricum 30X, Lycopodium Clavatum 30X, Phosphorus 30X, Pulsatilla 30X, Pyrogenium 30X, Sulphur 30X

INDICATIONS AND USAGE

USES: Temporarily relieves high fevers, fevers with sweat, fevers with sore throat, and/or remittent fevers.**

PURPOSE

USES: Temporarily relieves high fevers, fevers with sweat, fevers with sore throat, and/or remittent fevers.**

DOSAGE AND ADMINISTRATION

DIRECTIONS: 10 drops orally 3 times daily, or as directed by a health care professional.

KEEP OUT OF REACH OF CHILDREN

KEEP OUT OF THE REACH OF CHILDREN. In case of overdose (or accidental ingestion) get medical help or contact a Poison Control Center right away.

WARNINGS:

- Consult a physician for use in children under 12 years of age.
- IF PREGNANT OR BREAST-FEEDING, ask a health care professional before use.
- KEEP OUT OF THE REACH OF CHILDREN. In case of overdose (or accidental ingestion) get medical help or contact a Poison Control Center right away.
- Do not use if TAMPER EVIDENT seal is broken or missing.

INACTIVE INGREDIENT

INACTIVE INGREDIENTS: Citric Acid, Glycerin USP, Natural Cherry Flavor, Potassium Sorbate, Purified Water

QUESTIONS & COMMENTS?

Natural Creations, Inc. / Woodbine, IA 51579 / 712-647-1600

REFERENCES

*The letters "HPUS" indicate the components in the product are officially monographed in the Homeopathic Pharmacopeia of the United States.

**Claims based on traditional homeopathic practice, not accepted medical evidence. Not FDA evaluated.

PACKAGE LABEL

NDC:43406-0698-1

Fever CP

HOMEOPATHIC

1 fl oz (30mL) / Natural Cherry Flavor